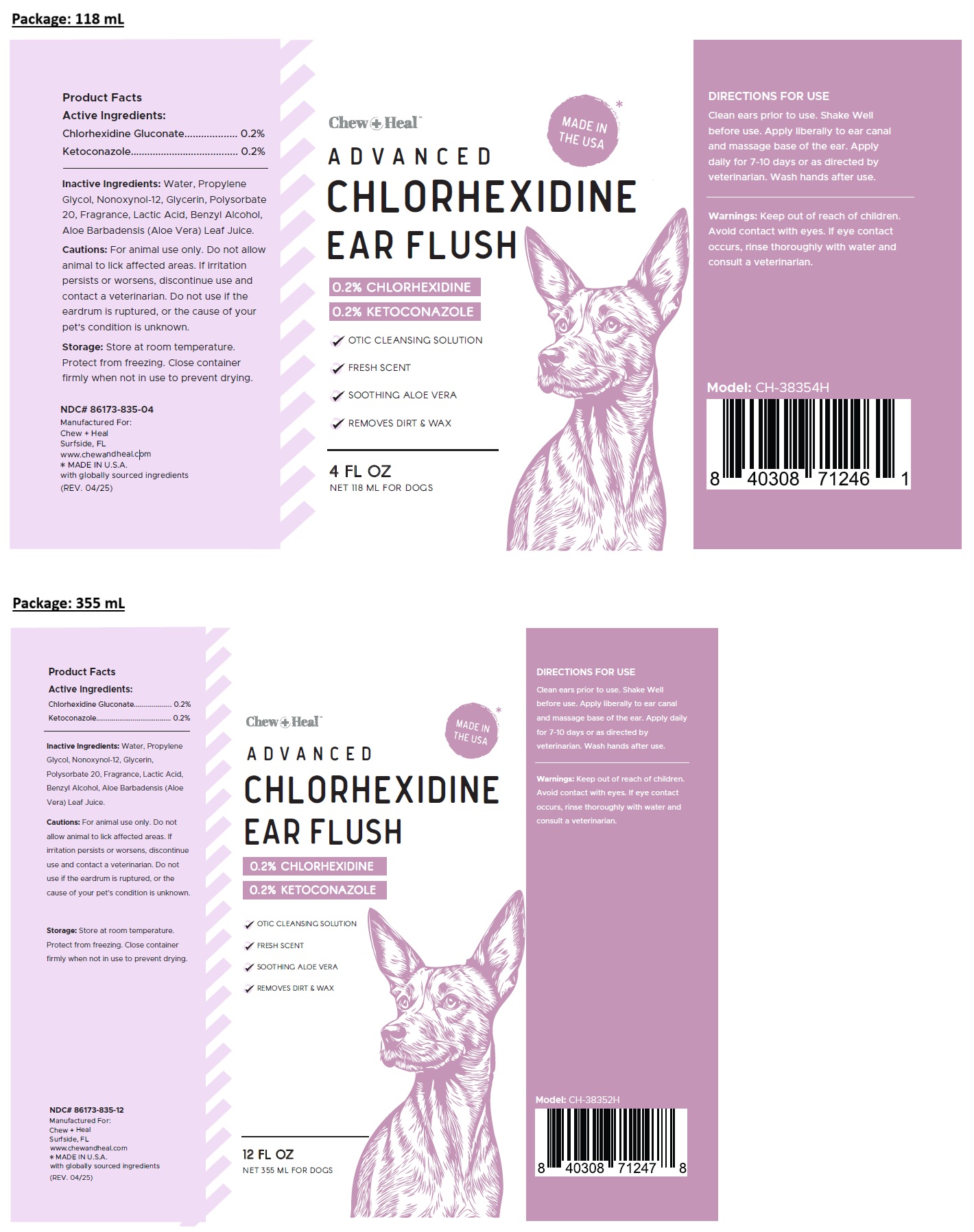 DRUG LABEL: Chew Plus Heal ADVANCED CHLORHEXIDINE EAR FLUSH
NDC: 86173-835 | Form: SOLUTION
Manufacturer: Click Industries LLC
Category: animal | Type: OTC ANIMAL DRUG LABEL
Date: 20250410

ACTIVE INGREDIENTS: CHLORHEXIDINE GLUCONATE 0.2 g/100 mL; KETOCONAZOLE 0.2 g/100 mL
INACTIVE INGREDIENTS: WATER; PROPYLENE GLYCOL; NONOXYNOL-12; GLYCERIN; POLYSORBATE 20; LACTIC ACID, UNSPECIFIED FORM; BENZYL ALCOHOL; ALOE VERA LEAF JUICE

Chew+Heal™ ADVANCED CHLORHEXIDINE EAR FLUSH

Active Ingredients:

Chlorhexidine Gluconate................... 0.2%
Ketoconazole....................................... 0.2%

Inactive Ingredients:

Water, Propylene Glycol, Nonoxynol-12, Glycerin, Polysorbate 20, Fragrance, Lactic Acid, Benzyl Alcohol, Aloe Barbadensis (Aloe Vera) Leaf Juice.

Cautions:

For animal use only. Do not allow animal to lick affected areas. If irritation persists or worsens, discontinue use and contact a veterinarian. Do not use if the eardrum is ruptured, or the cause of your pet's condition is unknown.

Storage:

Store at room temperature. Protect from freezing. Close container firmly when not in use to prevent drying.

DIRECTIONS FOR USE

Clean ears prior to use. Shake Well before use. Apply liberally to ear canal and massage base of the ear. Apply daily for 7-10 days or as directed by veterinarian. Wash hands after use.

Warnings:

Keep out of reach of children. Avoid contact with eyes. If eye contact occurs, rinse thoroughly with water and consult a veterinarian.

✓ OTIC CLEANSING SOLUTION

✓ FRESH SCENT

✓ SOOTHING ALOE VERA

✓ REMOVES DIRT & WAX

Manufactured For:
Chew + Heal
Surfside, FL
www.chewandheal.com
*MADE IN U.S.A.
with globally sourced ingredients